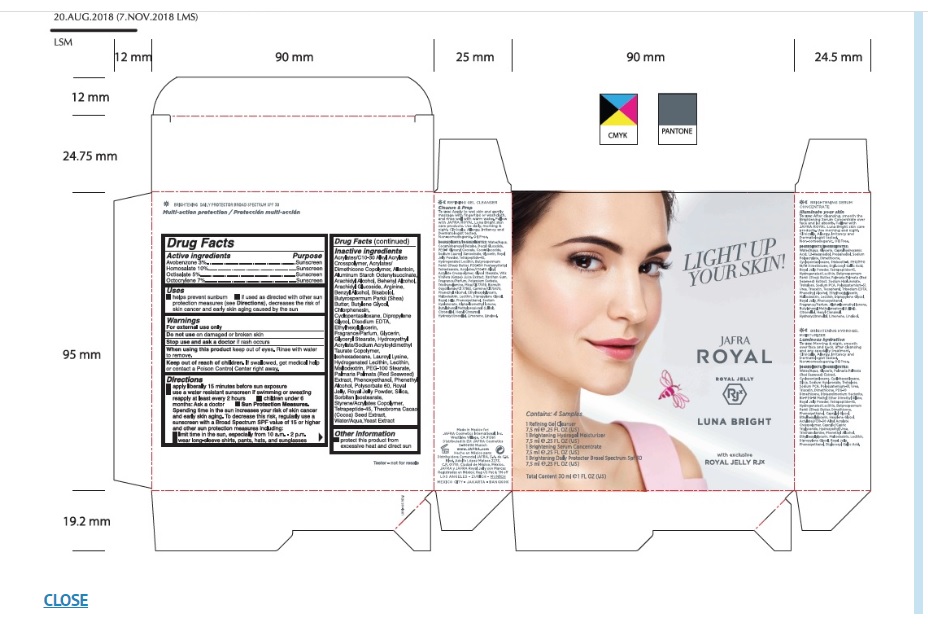 DRUG LABEL: Jafra Royal Luna Bright Kit
NDC: 68828-757 | Form: KIT | Route: TOPICAL
Manufacturer: JAFRA COSMETICS INTERNATIONAL INC
Category: otc | Type: HUMAN OTC DRUG LABEL
Date: 20230725

ACTIVE INGREDIENTS: AVOBENZONE 3 g/100 mL; HOMOSALATE 10 g/100 mL; OCTISALATE 5 g/100 mL; OCTOCRYLENE 7 g/100 mL
INACTIVE INGREDIENTS: HYDROXYETHYL ACRYLATE/SODIUM ACRYLOYLDIMETHYL TAURATE COPOLYMER (100000 MPA.S AT 1.5%); LAUROYL LYSINE; CARBOMER COPOLYMER TYPE A (ALLYL PENTAERYTHRITOL CROSSLINKED); ARACHIDYL ALCOHOL; DOCOSANOL; ARGININE; LEVOMENOL; SHEA BUTTER; BUTYLENE GLYCOL; CHLORPHENESIN; ETHYLHEXYLGLYCERIN; PHENOXYETHANOL; ALLANTOIN, (+)-; ALUMINUM STARCH OCTENYLSUCCINATE; ARACHIDYL GLUCOSIDE; BENZYL ALCOHOL; CYCLOMETHICONE 5; EDETATE DISODIUM; ISOHEXADECANE; HYDROGENATED SOYBEAN LECITHIN; LECITHIN, SOYBEAN; MALTODEXTRIN; PEG-100 STEARATE; DULSE; POLYSORBATE 60; ROYAL JELLY; SILICON DIOXIDE; PEG-20 SORBITAN ISOSTEARATE; COCOA; GLYCERYL MONOSTEARATE; GLYCERIN; WATER; DIPROPYLENE GLYCOL; PHENYLETHYL ALCOHOL

Jafra Royal Luna Bright Kit

Active Ingredient(s)

Avobenzone 3%

Homosalate 10%

Octisalate 5%

Octocrylene 7%

Purpose

Sunscreen

Uses

Helps prevent sunburn
If used as directed with other sun protection measures (see Directions), decreases the risk of skin cancer and early skin aging caused by the sun.

Warnings

For external use only

Do not useon damaged or broken skin

Stop use and ask a doctorif rash occurs

When using this productkeep out of eyes. Rinse with water to remove.

Keep out of reach of children.If swallowed, get medical help or contact a Poison Control Center right away.

Directions

- apply liberally 15 minutes before sun exposure
- use a water resistant sunscreen if swimming or sweating
- reapply at least every 2 hours
- children under 6 months: Ask a doctor
- Sun Protection Measures.Spending time in the sun increases your risk of skin cancer and early skin aging. To decrease this risk, regularly use a sunscreen with a Broad Spectrum SPF value of 15 or higher and other sun measures including:
- limit time in the sun, especially from 10 a.m. - 2 p.m.
- wear long-sleeve shirts, pants, hats, and sunglasses

Inactive ingredients

Acrylates/C10-30 Alkyl Acrylate Crosspolymer, Acrylates/Dimethicone Copolymer, Allantoin, Aluminum Starch Octenylsuccinate, Arachidyl Alcohol, Behenyl Alcohol, Arachidyl Glucoside, Arginine, Benzyl Alcohol, Bisabolol, Butyrospermum Parkii (Shea) Butter, Butylene Glycol, Chlorphenesin, Cyclopentasiloxane, Dipropylene Glycol, Disodium EDTA, Ethylhexylglycerin, Fragrance/Parfum, Glycerin, Glyceryl Stearate, Hydroxyethyl Acrylate/Sodium Acryloyldimethyl Taurate Copolymer, Isohexadecane, Lauroyl Lysine, Hydrogenated Lecithin, Lecithin, Maltodextrin, PEG-100 Stearate, Palmaria Palmata (red seaweed) Extract, Phenoxyethanol, Phenethyl Alcohol, Polysorbate 60, Royal Jelly, Royal Jelly Powder, Silica, Sorbitan Isostearate, Styrene/Acrylates Copolymer, Tetrapeptide-45, Theobroma Cacao (Cocoa) Seed Extract, Water/Aqua, Yeast Extract

Other information

Protect this product from excessive heat and direct sun